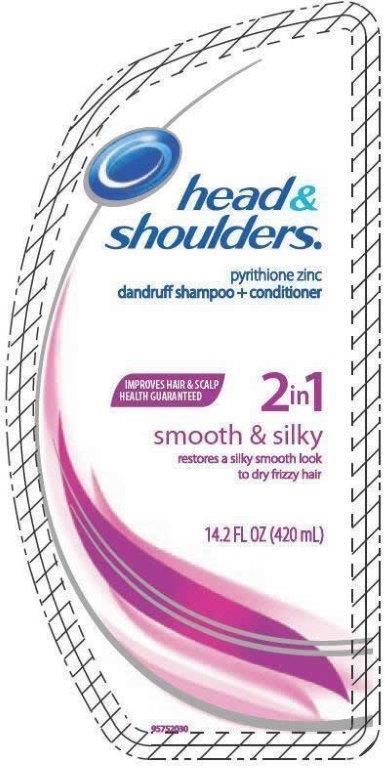 DRUG LABEL: Head And Shoulders
NDC: 69772-324 | Form: LOTION/SHAMPOO
Manufacturer: Teresa Cecena DBA Genesis
Category: otc | Type: HUMAN OTC DRUG LABEL
Date: 20170419

ACTIVE INGREDIENTS: PYRITHIONE ZINC 1 g/1 mL
INACTIVE INGREDIENTS: METHYLCHLOROISOTHIAZOLINONE; METHYLISOTHIAZOLINONE; SODIUM LAURETH-3 SULFATE; SODIUM LAURYL SULFATE; DIMETHICONE; COCO MONOETHANOLAMIDE; ZINC CARBONATE; GLYCOL DISTEARATE; SODIUM XYLENESULFONATE; CETYL ALCOHOL; MAGNESIUM SULFATE, UNSPECIFIED; SODIUM BENZOATE; MAGNESIUM CARBONATE HYDROXIDE; WATER; SODIUM CHLORIDE; BENZYL ALCOHOL

DRUG FACTS

ACTIVE INGREDIENTE

Pyrithione Zinc 1%

PURPOSE

Anti-drandruff

USES

Help prevent recurrence of flaking and itching associated with dandruff

WARNINGS

FOR EXTERNAL USE ONLY

WHEN USING THIS PRODUCT

- Avoid contact with eyes. If contact occurs, rinse eyes thoroughly with water
- STOP USE AND ASK A DOCTOR IF: condition worsens or does not improve after regular use of this product as directed.

KEEP OUT OF REACH OF CHILDREN

KEEP THIS AND ALL DRUGS OUT OF REACH OF CHILDREN. If swallowed, get medical help or contact a poison control center right away

DIRECTIONS

- For maximun drandruff contral, use every time you shampoo.
- Wet hair, massage onto scalp, rinse, repeat if desired.
- For best results use at least twice a week or as directed by a doctor.

INACTIVE INGREDIENT

Water, soium laureth sulfate, sodium lauryl sulfate, dimethicone, cocamide MEA, zinc carbonate, glycoldistearate, sodium xylenesulfonate, fragance, cethyl alcohol, guar hydroxypropyltrimonium chloride, magnesium sulfate, sodium chloride, sodium benzoate, magnesium carbonate hydroxide, benzyl alcohol, methylchloroisothiazolinone, methlylisothiazolinone.

Made in Mexico By:

Procter and Gamble

#69772

INDICATIONS AND USAGE

FOR EXTERNAL USE ONLY

FOR BEST RESULT USE AT LEAST TWICE A WEEK OR AS DIRECTED BY A DOCTOR

PACKAGE LABEL

Shoulder